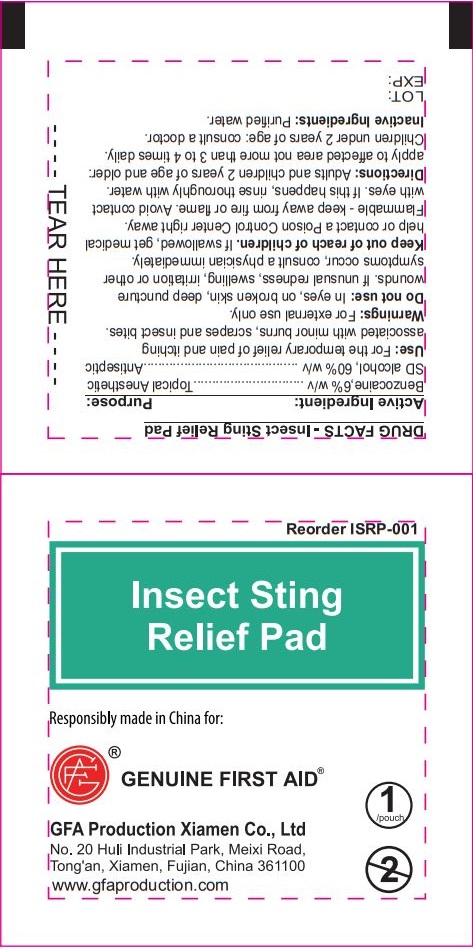 DRUG LABEL: Genuine First Aid Insect Sting Relief Pad 1 ct
NDC: 50814-065 | Form: SWAB
Manufacturer: GFA Production (Xiamen) Co., Ltd.
Category: otc | Type: HUMAN OTC DRUG LABEL
Date: 20241015

ACTIVE INGREDIENTS: BENZOCAINE 60 mg/1 mL; ALCOHOL 600 mg/1 mL
INACTIVE INGREDIENTS: WATER

Genuine First Aid Insect Sting Relief Pad 1 ct

Active Ingredient:

Benzocaine , 6% w/v

SD alcohol, 60%

Purpose:

Topical Anesthetic

Antiseptic

Use:

For the temporary relief of pain and itching associated with minor burns, scrapes and insect bites.

Warnings:

For external use only.

Do not use:

In eyes, on broken skin, deep puncture wounds. If unusual redness, swelling, irritation or other symptoms occur, consult a physician immediately.

Keep out of reach of children.

If swallowed, get medical help or contact a Poison Control Center right away.

Flammable - keep away from fire or flame. Avoid contact with eyes. If this happens, rinse thoroughly with water.

Directions:

Adults and children 2 years of age and older: apply to affected area not more than 3 to 4 times daily. Children under 2 years of age: consult a doctor.

Inactive Ingredients:

Purified water.